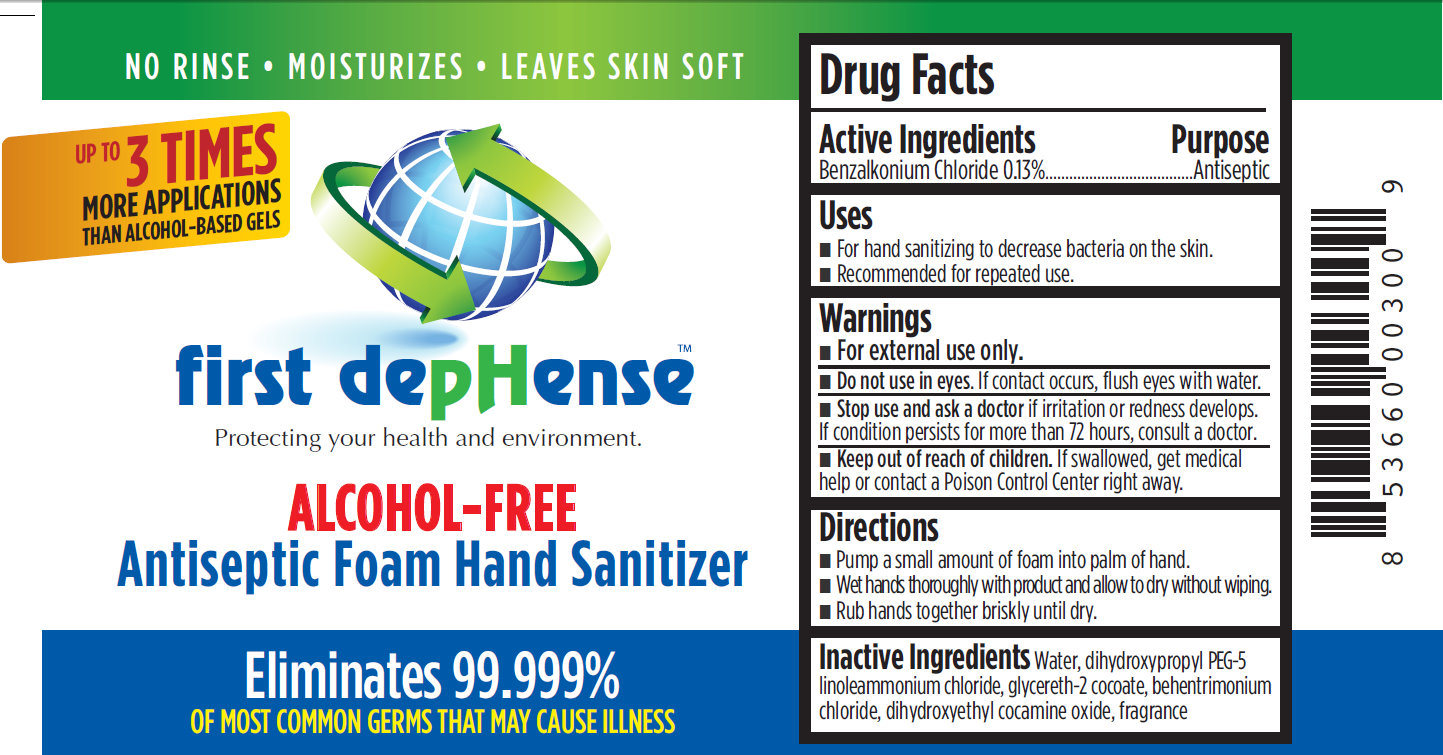 DRUG LABEL: first depHense Alcohol-Free Antiseptic Foam Hand Sanitizer
NDC: 76116-100 | Form: LIQUID
Manufacturer: First Dephense, LLC
Category: otc | Type: HUMAN OTC DRUG LABEL
Date: 20110328

ACTIVE INGREDIENTS: BENZALKONIUM CHLORIDE 0.13 mL/100 mL
INACTIVE INGREDIENTS: WATER; DIHYDROXYPROPYL PEG-5 LINOLEAMMONIUM CHLORIDE; GLYCERETH-2 COCOATE; BEHENTRIMONIUM CHLORIDE; DIHYDROXYETHYL COCAMINE OXIDE

first depHense ALCOHOL-FREE Antiseptic Foam Hand Sanitizer

Drug Facts

Active Ingredients

Benzalkonium Chloride 0.13%

Purpose

Antimicrobial

Uses

- For hand sanitizing to decrease bacteria on the skin
- Recommended for repeated use

Warnings

- For external use only.

- Do not use in eyes. If contact occurs, flush eyes with water.

- Stop use and ask a doctor if irritation or redness develops. If condition persists for more than 72 hours, consult a doctor.

- Keep out of reach of children. If swallowed, get medical help or contact a Poison Control Center right away.

Directions

- Pump a small amount of foam into palm of hand.
- Wet hands thoroughly with product and allow to dry without wiping.
- Rub hands together briskly until dry.

Inactive Ingredients

Water, dihydroxypropyl PEG-5 linoleammonium chloride, glycereth-2cocoate, behentrimonium chloride, dihydroxyethyl cocamine oxide, fragrance

Distributed by first depHense, LLC
519 S. Main St., Sycamore, IL 60178

Made in USA.

PACKAGE LABEL

- NO RINSE
- MOISTURIZES
- LEAVES SKIN SOFT

Up To 3 Times MORE APPLICATIONS
THAN ALCOHOL-BASED GELS
first depHense
Protecting your health and environment
ALCOHOL-FREE
Antiseptic Foam Hand Sanitizer
Eliminates 99.999%
OF MOST COMMON GERMS THAT MAY CAUSE ILLNESS
Environmentally Friendly
1.7 floz (50ml)